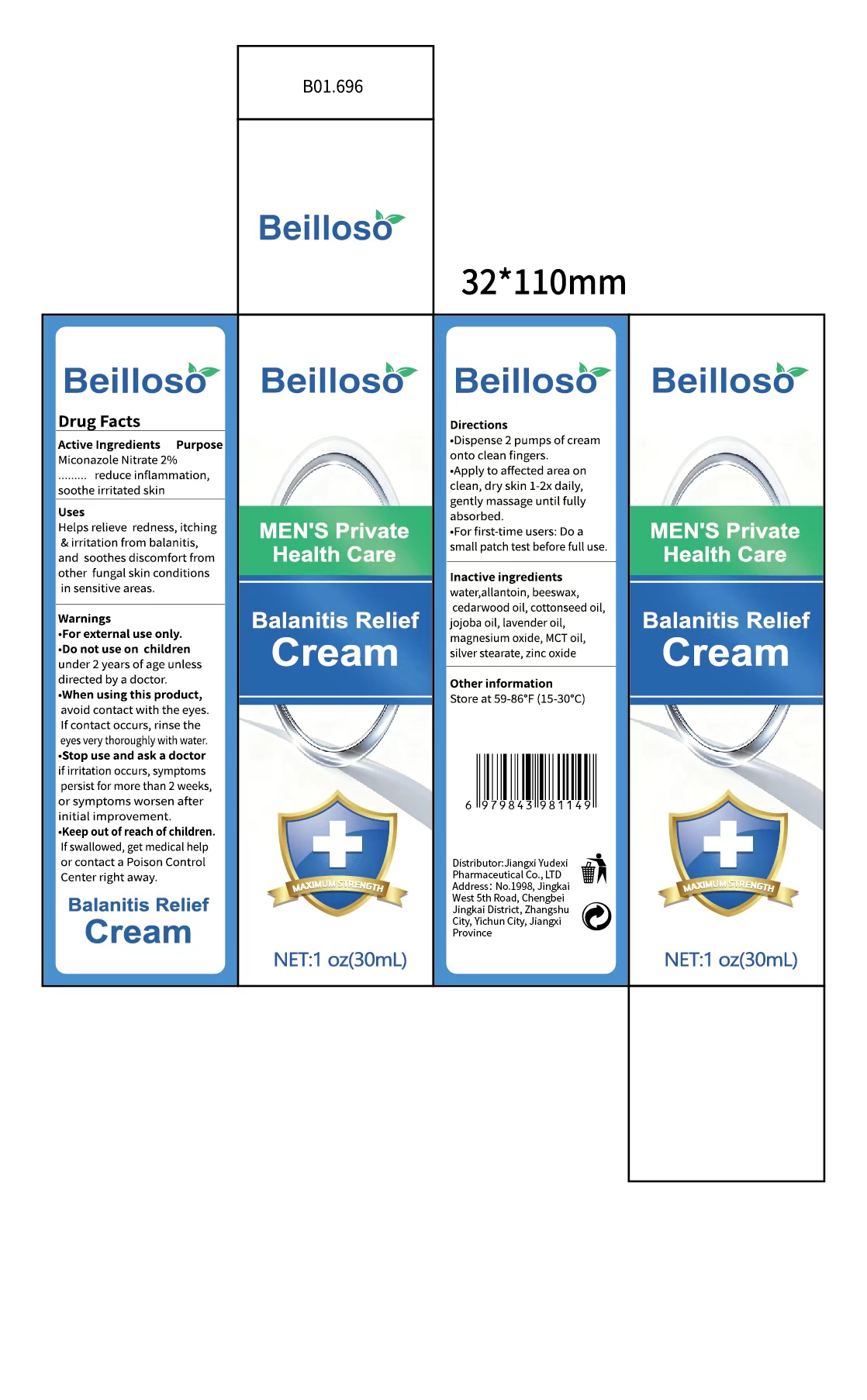 DRUG LABEL: Beilloso Balanitis Relief
NDC: 85248-138 | Form: CREAM
Manufacturer: Jiangxi Yudexi Pharmaceutical Co., LTD
Category: otc | Type: HUMAN OTC DRUG LABEL
Date: 20260209

ACTIVE INGREDIENTS: MICONAZOLE NITRATE 2 g/100 mL
INACTIVE INGREDIENTS: ALLANTOIN; LAVENDER OIL; WATER; JOJOBA OIL; ZINC OXIDE; MAGNESIUM OXIDE; SILVER STEARATE; MEDIUM-CHAIN TRIGLYCERIDES; COTTONSEED OIL; BEESWAX; CEDRUS ATLANTICA BARK OIL

85248-138

Active Ingredient

Miconazole Nitrate 2%

Purpose

reduce inflammation.soothe irritated skin

Use

Helps relieve redness, itching & irritation from balanitis,and soothes discomfort from other fungal skin conditions in sensitive areas.

Warnings

For external use only.

Do not use

under 2 years of age unless directed by a doctor.

When Using

avoid contact with the eyes.If contact occurs. rinse the eyes very thoroughly with water

Stop Use

if irritation occurs,symptoms perist for more than 2 weeks,or symptoms worsen after initial improvement.

Ask Doctor

if irritation occurs,symptoms perist for more than 2 weeks,or symptoms worsen after initial improvement.

Keep Oot Of Reach Of Children

lf swallowed. get medical help or contact a Poison Control Center right away.

Directions

·Dispense 2 pumps of cream onto clean fingers.·Apply to affected area on clean, dry skin 1-2x daily,gently massage until fully absorbed.·For first-time users: Do a small patch test before full use

Other information

Store at 59-86°F(15-30°C）

Inactive ingredients

water,allantoin.beeswax,cedarwood oil, cottonseed oil, jojoba oil lavender oil, magnesium oxide,MCT oil, silver stearate, zinc oxide.